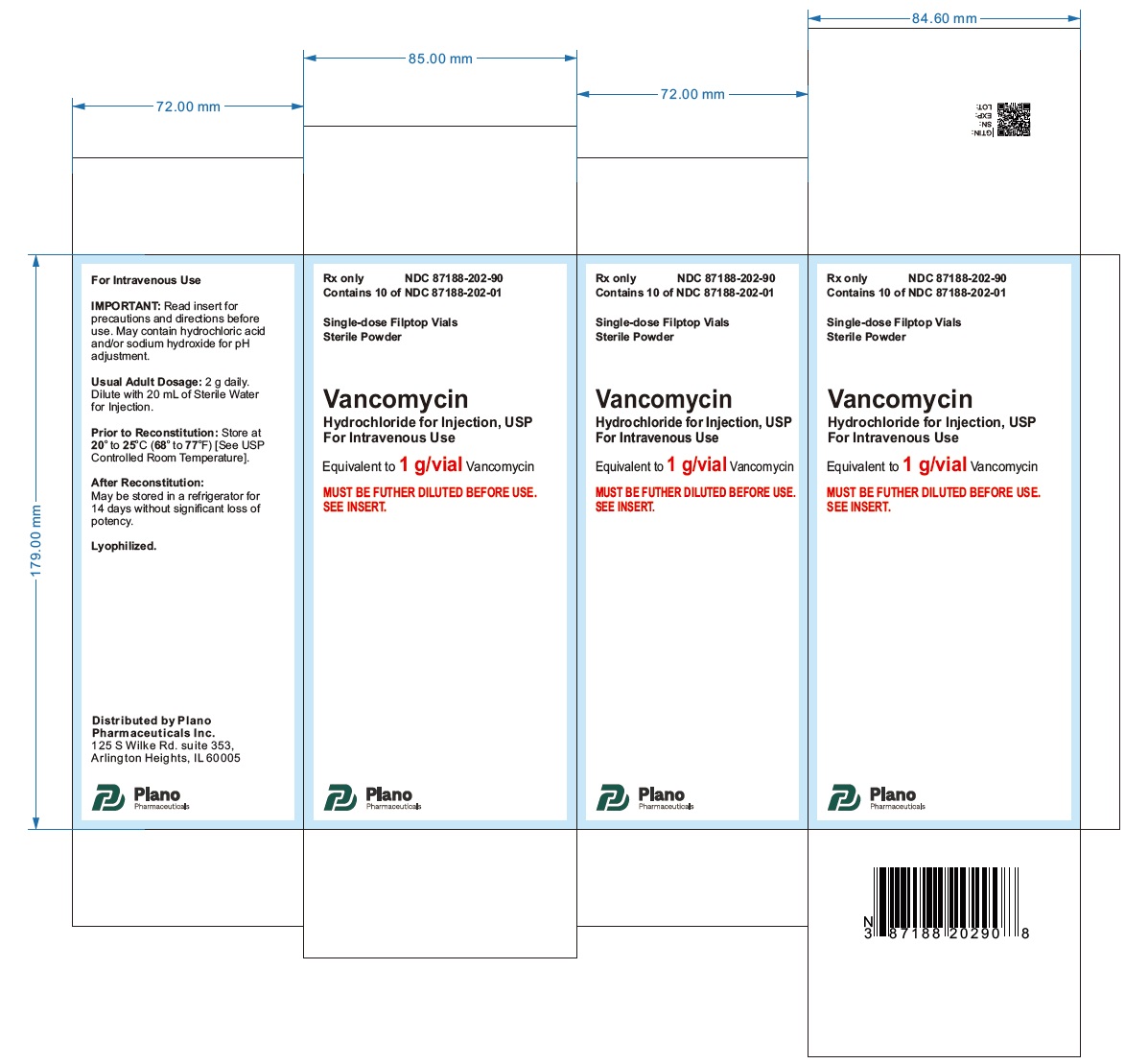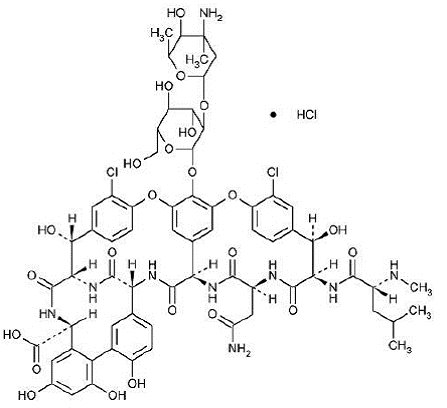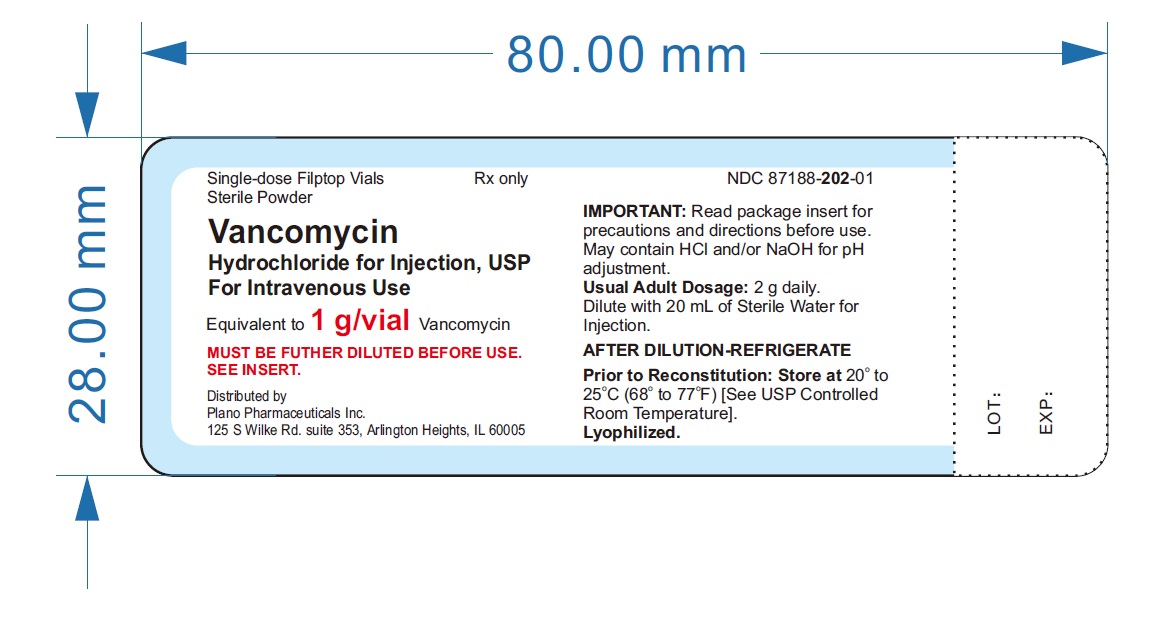 DRUG LABEL: Vancomycin Hydrochloride
NDC: 87188-202 | Form: INJECTION, POWDER, LYOPHILIZED, FOR SOLUTION
Manufacturer: Plano Pharmaceuticals Inc.
Category: prescription | Type: HUMAN PRESCRIPTION DRUG LABEL
Date: 20260224

ACTIVE INGREDIENTS: VANCOMYCIN HYDROCHLORIDE 1 g/20 mL
INACTIVE INGREDIENTS: HYDROCHLORIC ACID; SODIUM HYDROXIDE

Vancomycin Hydrochloride for Injection, USP
Fliptop Vial for Intravenous Use

To reduce the development of drug-resistant bacteria and maintain the effectiveness of vancomycin hydrochloride for injection and other antibacterial drugs, vancomycin hydrochloride for injection should be used only to treat or prevent infections that are proven or strongly suspected to be caused by bacteria.

DESCRIPTION

Vancomycin hydrochloride for injection, USP is a lyophilized powder, for preparing intravenous (IV) infusions, in vials each containing the equivalent of 500 mg or 1 g vancomycin base. 500 mg of the base are equivalent to 0.34 mmol and 1 g of the base are equivalent to 0.67 mmol. When reconstituted with Sterile Water for Injection to a concentration of 50 mg/mL, the pH of the solution is between 2.5 and 4.5. This product is oxygen sensitive. Vancomycin Hydrochloride for Injection, USP should be administered intravenously in diluted solution (see DOSAGE AND ADMINISTRATION), AFTER RECONSTITUTION FURTHER DILUTION IS REQUIRED BEFORE USE.

Vancomycin is a tricyclic glycopeptide antibiotic derived from Amycolatopasis orientalis (formerly Nocardia orientals). The chemical name for vancomycin hydrochloride is 3S- [3R*,6S*(S*),7S*,22S*,23R*,26R*,36S*,38aS*]]-3-(2-Amino-2-oxoethyl)-44-[[2-O-(3-amino-2,3,6-trideoxy-3-C-methyl--L-lyxo-hexopyranosyl)--D-glucopyranosyl]oxy]-10,19-dichloro-2,3,4,5,6,7,23,24,25,26,36, 37,38,38a-tetradecahydro-7,22,28,30,32-pentahydroxy-6-[[4-methyl-2-(methylamino)-1-oxopentyl]amino]-2,5,24,38,39-pentaoxo-22H-8,11:18,21-dietheno-23,36-(iminomethano)-13,16:31,35-dimetheno-1H,16H-[1,6,9]oxadiazacyclohexadecino[4,5-m][10,2,16]-benzoxadiazacyclotetracosine-26-carboxylic acid, monohydrochloride. The molecular formula is C66H75Cl2N9O24• HCl and the molecular weight is 1,485.74.

Vancomycin hydrochloride has the following structural formula:

CLINICAL PHARMACOLOGY

Vancomycin is poorly absorbed after oral administration.

In subjects with normal kidney function, multiple intravenous dosing of 1 g of vancomycin (15 mg/kg) infused over 60 minutes produces mean plasma concentrations of approximately 63 mcg/mL immediately after the completion of infusion, mean plasma concentrations of approximately 23 mcg/mL 2 hours after infusion, and mean plasma concentrations of approximately 8 mcg/mL 11 hours after the end of the infusion. Multiple dosing of 500 mg infused over 30 minutes produces mean plasma concentrations of about 49 mcg/mL at the completion of infusion, mean plasma concentrations of about 19 mcg/mL 2 hours after infusion, and mean plasma concentrations of about 10 mcg/mL 6 hours after infusion. The plasma concentrations during multiple dosing are similar to those after a single dose.

The mean elimination half-life of vancomycin from plasma is 4 to 6 hours in subjects with normal renal function. In the first 24 hours, about 75% of an administered dose of vancomycin is excreted in urine by glomerular filtration. Mean plasma clearance is about 0.058 L/kg/h, and mean renal clearance is about 0.048 L/kg/h. Renal dysfunction slows excretion of vancomycin. In anephric patients, the average half-life of elimination is 7.5 days. The distribution coefficient is from 0.3 to 0.43 L/kg. There is no apparent metabolism of the drug. About 60% of an intraperitoneal dose of vancomycin administered during peritoneal dialysis is absorbed systemically in 6 hours. Serum concentrations of about 10 mcg/mL are achieved by intraperitoneal injection of 30 mg/kg of vancomycin. However, the safety and efficacy of the intraperitoneal use of vancomycin has not been established in adequate and well-controlled trials (see PRECAUTIONS).

Total systemic and renal clearance of vancomycin may be reduced in the elderly. Vancomycin is approximately 55% serum protein bound as measured by ultrafiltration at vancomycin serum concentrations of 10 to 100 mcg/mL. After IV administration of vancomycin, inhibitory concentrations are present in pleural, pericardial, ascitic, and synovial fluids; in urine; in peritoneal dialysis fluid; and in atrial appendage tissue. Vancomycin does not readily diffuse across normal meninges into the spinal fluid; but, when the meninges are inflamed, penetration into the spinal fluid occurs.

Microbiology

The bactericidal action of vancomycin results primarily from inhibition of cell-wall biosynthesis. In addition, vancomycin alters bacterial-cell-membrane permeability and RNA synthesis. There is no cross-resistance between vancomycin and other antibiotics. Vancomycin is not active in vitroagainst gram-negative bacilli, mycobacteria, or fungi.

Synergy

The combination of vancomycin and an aminoglycoside acts synergistically in vitroagainst many strains of Staphylococcus aureus, Streptococcus bovis,enterococci, and the viridans group streptococci.

Vancomycin has been shown to be active against most strains of the following microorganisms, both in vitroand in clinical infections as described in the INDICATIONS AND USAGEsection.

Aerobic gram-positive microorganisms

Diphtheroids

Enterococci (e.g., Enterococcus faecalis)

Staphylococci, including Staphylococcus aureusand Staphylococcus epidermidis

(including heterogeneous methicillin-resistant strains)

Streptococcus bovis

Viridans group streptococci

The following in vitrodata are available, but their clinical significance is unknown.

Vancomycin exhibits in vitroMIC’s of 1 mcg/mL or less against most (≥90%) strains of streptococci listed below and MIC’s of 4 mcg/mL or less against most (≥90%) strains of other listed microorganisms; however, the safety and effectiveness of vancomycin in treating clinical infections due to these microorganisms have not been established in adequate and well- controlled clinical trials.

Aerobic gram-positive microorganisms

Listeria monocytogenes Streptococcus pyogenes Streptococcus pneumoniae(including penicillin-resistant strains) Streptococcus agalactiae

Anaerobic gram-positive microorganisms

Actinomycesspecies

Lactobacillusspecies

Susceptibility Test Methods

When available, the clinical microbiology laboratory should provide the results of in vitrosusceptibility test results for antimicrobial drugs used in local hospitals and practice areas to the physician as periodic reports that describe the susceptibility profile of nosocomial and community-acquired pathogens. These reports should aid the physician in selecting the most effective antimicrobial.

Dilution Techniques

Quantitative methods are used to determine antimicrobial minimum inhibitory concentrations (MICs). These MICs provide estimates of the susceptibility of bacteria to antimicrobial compounds. The MICs should be determined using a standardized procedure. Standardized procedures are based on dilution method^1,2(broth, agar or microdilution) or equivalent using standardized inoculum and concentrations of vancomycin powder. The MIC values should be interpreted according to the criteria in Table 1.

Diffusion Techniques

Quantitative methods that require measurement of zone diameters also provide reproducible estimates of the susceptibility of bacteria to antimicrobial compounds. One such standardized procedure^2,3requires the use of standardized inoculum concentrations. This procedure uses paper disks impregnated with 30 mcg of vancomycin to test the susceptibility of microorganisms to vancomycin. Interpretation involves correlation of the diameter obtained in the disk test with the MIC for vancomycin.

Reports from the laboratory providing results of the standard single-disk susceptibility test with a 30 mcg vancomycin disk should be interpreted according to the following criteria in Table 1.

Table 1: Susceptibility Test Interpretive Criteria for Vancomycin
Pathogen | Minimum Inhibitory Concentrations (mcg/mL) |  |  | Disk Diffusion Diameters (mm)
Pathogen | Susceptible (S) | Intermediate (I) | Resistant (R) | Susceptible (S) | Intermediate (I) | Resistant (R)
Enterococci | ≤4 | 8 to 16 [Isolates with vancomycin MICs of 8 to 16 mcg/mL should be further screened for vancomycin resistance using standardized procedures. 1,2] | ≥32 | ≥17 [Plates should be held for a full 24 hours and examined using transmitted light. Measure the diameter of complete inhibition (as judged by the unaided eye), including the diameter of the disk. The zone margin should be considered the area showing no obvious, visible growth that can be detected only with the unaided eye. Ignore faint growth or tiny colonies that can be detected only with a magnifying lens at the edge of the zone of inhibited growth. Any discernible growth within the zone of inhibition indicates vancomycin resistance. Organisms with intermediate zones should be tested by a standardized dilution method. 1,2] | 15 to 16 | ≤14
Staphylococcus aureus [Dilution testing should be performed to determine the susceptibility of all staphylococcal isolates. Disk diffusion testing is not reliable for testing vancomycin, as it does not differentiate vancomycin-susceptible isolates of S. aureus from vancomycin-intermediate isolates, nor does it differentiate among vancomycin-susceptible, intermediate, and resistant isolates of coagulase-negative staphylococci. 2] , [Any S. aureusisolate for which the vancomycin MIC is ≥ 8 mcg/mL should be sent to a reference laboratory.2] | ≤2 | 4 to 8 | ≥16 | — | — | —
Coagulase-negative staphylococci , [Any coagulase-negative Staphylococcusisolate for which the vancomycin MIC is ≥ 32 mcg/mL should be sent to a reference laboratory.2] | ≤4 | 8 to 16 | ≥32 | — | — | —
Streptococci spp. other than S. pneumoniae | ≤1 [The rare occurrence of resistant isolates precludes defining any results categories other than “Susceptible”. For isolates yielding results suggestive of a nonsusceptible category, organism identification and vancomycin susceptibility test results should be confirmed. If confirmed, isolates should be sent to a reference laboratory. 2] , [Interpretative criteria applicable only to tests performed by broth microdilution method using cation-adjusted Mueller-Hinton broth with 2 to 5% lysed horse blood. 1,2] | — | — | ≥17 , [Interpretative criteria applicable only to tests performed by disk diffusion method using Mueler-Hinton agar with 5% defibrinated sheep blood and incubated in 5% CO 2. 3] | — | —

A report of "Susceptible" indicates that the pathogen is likely to be inhibited if the antimicrobial compound in the blood reaches the concentrations usually achievable. A report of "Intermediate" indicates that the result should be considered equivocal, and, if the microorganism is not fully susceptible to alternative, clinically feasible drugs, the test should be repeated. This category implies possible clinical applicability in body sites where the drug is physiologically concentrated or in situations where high dosage of drug can be used. This category also provides a buffer zone which prevents small uncontrolled technical factors from causing major discrepancies in interpretation. A report of "Resistant" indicates that the pathogen is not likely to be inhibited if the antimicrobial compound in the blood reaches the concentrations usually achievable; other therapy should be selected.

Quality Control

Standardized susceptibility test procedures require the use of laboratory control microorganisms to monitor and ensure the accuracy and precision of the supplies and reagents used in the assay, and the techniques of the individuals performing the test. When tested against appropriate quality control strains, standard vancomycin powder should provide MIC values shown in Table 2. For the diffusion technique, the 30 mcg vancomycin disk should provide the zone diameters in Table 2with the quality control strains:

Table 2: In Vitro Susceptibility Test Quality Control Ranges for Vancomycin
Organism (ATCC #) | MIC range (mcg/mL) | Disk diffusion range (mm)
Enterococcus faecalis(29212) | 1 to 4 | Not applicable
Staphylococcus aureus(29213) | 0.5 to 2 | Not applicable
Staphylococcus aureus(25923) [Quality control strain and interpretative criteria for testing vancomycin susceptibility of enterococci spp.] | Not applicable | 17 to 21
Streptococcus pneumoniae (49619) [Interpretative criteria applicable only to tests performed using cation-adjusted Mueller-Hinton broth with 2 to 5% lysed horse blood 1. Disk diffusion interpretative criteria applicable only to tests performed using Mueller-Hinton agar with 5% defibrinated sheep blood and incubated in 5% CO 22] [Quality control strain and interpretative criteria for testing vancomycin susceptibility of Streptococci spp. other than S. pneumoniae.] | 0.12 to 0.5 | 20 to 27

INDICATIONS AND USAGE

Vancomycin hydrochloride for injection is indicated for the treatment of serious or severe infections caused by susceptible strains of methicillin-resistant (β-lactam-resistant) staphylococci. It is indicated for penicillin-allergic patients, for patients who cannot receive or who have failed to respond to other drugs, including the penicillins or cephalosporins, and for infections caused by vancomycin-susceptible organisms that are resistant to other antimicrobial drugs. Vancomycin hydrochloride for injection, USP is indicated for initial therapy when methicillin-resistant staphylococci are suspected, but after susceptibility data are available, therapy should be adjusted accordingly.

Vancomycin hydrochloride for injection is effective in the treatment of staphylococcal endocarditis. Its effectiveness has been documented in other infections due to staphylococci, including septicemia, bone infections, lower respiratory tract infections, skin and skin structure infections. When staphylococcal infections are localized and purulent, antibiotics are used as adjuncts to appropriate surgical measures.

Vancomycin hydrochloride for injection has been reported to be effective alone or in combination with an aminoglycoside for endocarditis caused by S. viridans or S. bovis. For endocarditis caused by enterococci (e.g., E. faecalis), vancomycin has been reported to be effective only in combination with an aminoglycoside.

Vancomycin hydrochloride for injection has been reported to be effective for the treatment of diphtheroid endocarditis. Vancomycin hydrochloride for injection has been used successfully in combination with either rifampin, an aminoglycoside, or both in early-onset prosthetic valve endocarditis caused by S. epidermidis or diphtheroids.

Specimens for bacteriologic cultures should be obtained in order to isolate and identify causative organisms and to determine their susceptibilities to vancomycin.

To reduce the development of drug-resistant bacteria and maintain the effectiveness of vancomycin hydrochloride for injection and other antibacterial drugs, vancomycin hydrochloride for injection should be used only to treat or prevent infections that are proven or strongly suspected to be caused by susceptible bacteria. When culture and susceptibility information are available, they should be considered in selecting or modifying antibacterial therapy. In the absence of such data, local epidemiology and susceptibility patterns may contribute to the empiric selection of therapy.

The parenteral form of vancomycin hydrochloride may be administered orally for treatment of antibiotic-associated pseudomembranous colitis produced by C. difficile and for staphylococcal enterocolitis. Parenteral administration of vancomycin hydrochloride alone is of unproven benefit for these indications. Vancomycin is not effective by the oral route for other types of infections.

CONTRAINDICATIONS

Vancomycin hydrochloride for injection is contraindicated in patients with known hypersensitivity to this antibiotic.

WARNINGS

Rapid bolus administration (e.g., over several minutes) may be associated with exaggerated hypotension, including shock and rarely cardiac arrest.

Vancomycin hydrochloride for injection should be administered in a diluted solution over a period of not less than 60 minutes to avoid rapid-infusion-related reactions. Stopping the infusion usually results in prompt cessation of these reactions.

Ototoxicity has occurred in patients receiving vancomycin hydrochloride for injection. It may be transient or permanent. It has been reported mostly in patients who have been given excessive doses, who have an underlying hearing loss, or who are receiving concomitant therapy with another ototoxic agent, such as an aminoglycoside. Vancomycin should be used with caution in patients with renal insufficiency because the risk of toxicity is appreciably increased by high, prolonged blood concentrations.

Dosage of vancomycin hydrochloride for injection must be adjusted for patients with renal dysfunction (see PRECAUTIONSand DOSAGE AND ADMINISTRATION).

Clostridium difficile associated diarrhea (CDAD) has been reported with use of nearly all antibacterial agents, including vancomycin hydrochloride for injection, and may range in severity from mild diarrhea to fatal colitis. Treatment with antibacterial agents alters the normal flora of the colon leading to overgrowth of C. difficile.

C. difficile produces toxins A and B which contribute to the development of CDAD. Hypertoxin producing strains of C. difficilecause increased morbidity and mortality, as these infections can be refractory to antimicrobial therapy and may require colectomy. CDAD must be considered in all patients who present with diarrhea following antibiotic use. Careful medical history is necessary since CDAD has been reported to occur over two months after the administration of antibacterial agents.

If CDAD is suspected or confirmed, ongoing antibiotic use not directed against C. difficilemay need to be discontinued. Appropriate fluid and electrolyte management, protein supplementation, antibiotic treatment of C. difficile,and surgical evaluation should be instituted as clinically indicated.

PRECAUTIONS

General

Clinically significant serum concentrations have been reported in some patients being treated for active C. difficile-induced pseudomembranous colitis after multiple oral doses of vancomycin.

Prolonged use of vancomycin hydrochloride for injection may result in the overgrowth of nonsusceptible microorganisms. Careful observation of the patient is essential. If superinfection occurs during therapy, appropriate measures should be taken. In rare instances, there have been reports of pseudomembranous colitis due to C. difficiledeveloping in patients who received intravenous vancomycin hydrochloride for injection.

In order to minimize the risk of nephrotoxicity when treating patients with underlying renal dysfunction or patients receiving concomitant therapy with an aminoglycoside, serial monitoring of renal function should be performed and particular care should be taken in following appropriate dosing schedules (see DOSAGE AND ADMINISTRATION).

Serial tests of auditory function may be helpful in order to minimize the risk of ototoxicity.

Reversible neutropenia has been reported in patients receiving vancomycin hydrochloride for injection (see ADVERSE REACTIONS). Patients who will undergo prolonged therapy with vancomycin hydrochloride or those who are receiving concomitant drugs that may cause neutropenia should have periodic monitoring of the leukocyte count.

Vancomycin hydrochloride for injection is irritating to tissue and must be given by a secure IV route of administration. Pain, tenderness, and necrosis occur with intramuscular (IM) injection of vancomycin hydrochloride for injection or with inadvertent extravasation. Thrombophlebitis may occur, the frequency and severity of which can be minimized by administering the drug slowly as a dilute solution (2.5 to 5 g/L) and by rotation of venous access sites.

There have been reports that the frequency of infusion-related events (including hypotension, flushing, erythema, urticaria, and pruritus) increases with the concomitant administration of anesthetic agents. Infusion-related events may be minimized by the administration of vancomycin as a 60-minute infusion prior to anesthetic induction. The safety and efficacy of vancomycin administered by the intrathecal (intralumbar or intraventricular) route or by the intraperitoneal route have not been established by adequate and well-controlled trials.

Although the safety and efficacy of vancomycin by the intraperitoneal route have not been established, reports have revealed that administration of sterile vancomycin by the intraperitoneal route during continuous ambulatory peritoneal dialysis (CAPD) has resulted in a syndrome of chemical peritonitis. To date, this syndrome has ranged from cloudy dialysate alone to a cloudy dialysate accompanied by variable degrees of abdominal pain and fever. This syndrome appears to be short-lived after discontinuation of intraperitoneal vancomycin.

Prescribing vancomycin hydrochloride for injection, USP in the absence of a proven or strongly suspected bacterial infection or a prophylactic indication is unlikely to provide benefit to the patient and increases the risk of the development of drug-resistant bacteria.

Drug Interactions

Concomitant administration of vancomycin and anesthetic agents has been associated with erythema and histamine-like flushing (see Pediatrics Useunder PRECAUTIONS) and anaphylactoid reactions (see ADVERSE REACTIONS).

Concurrent and/or sequential systemic or topical use of other potentially neurotoxic and/or nephrotoxic drugs, such as amphotericin B, aminoglycosides, bacitracin, polymixin B, colistin, viomycin, or cisplatin, when indicated, requires careful monitoring.

Carcinogenesis, Mutagenesis, Impairment of Fertility

Although no long-term studies in animals have been performed to evaluate carcinogenic potential, no mutagenic potential of vancomycin hydrochloride for injection was found in standard laboratory tests. No definitive fertility studies have been performed.

Pregnancy

Teratogenic Effects

Pregnancy Category C

Animal reproduction studies have not been conducted with vancomycin. It is not known whether vancomycin can affect reproduction capacity. In a controlled clinical study, the potential ototoxic and nephrotoxic effects of vancomycin on infants were evaluated when the drug was administered to pregnant women for serious staphylococcal infections complicating intravenous drug abuse. Vancomycin was found in cord blood. No sensorineural hearing loss or nephrotoxicity attributable to vancomycin was noted. One infant whose mother received vancomycin in the third trimester experienced conductive hearing loss that was not attributed to the administration of vancomycin. Because the number of patients treated in this study was limited and vancomycin was administered only in the second and third trimesters, it is not known whether vancomycin causes fetal harm. Vancomycin should be given to a pregnant woman only if clearly needed.

Nursing Mothers

Vancomycin hydrochloride for injection is excreted in human milk. Caution should be exercised when vancomycin hydrochloride for injection is administered to a nursing woman. Because of the potential for adverse events, a decision should be made whether to discontinue nursing or to discontinue the drug, taking into account the importance of the drug to the mother.

Pediatric Use

In pediatric patients, it may be appropriate to confirm desired vancomycin serum concentrations. Concomitant administration of vancomycin and anesthetic agents has been associated with erythema and histamine-like flushing in pediatric patients (see PRECAUTIONS).

Geriatric Use

The natural decrement of glomerular filtration with increasing age may lead to elevated vancomycin serum concentrations if dosage is not adjusted. Vancomycin dosage schedules should be adjusted in elderly patients (see DOSAGE AND ADMINISTRATION).

Information for Patients

Patients should be counseled that antibacterial drugs including vancomycin hydrochloride for injection, USP should only be used to treat bacterial infections. They do not treat viral infections (e.g., the common cold). When vancomycin hydrochloride for injection, USP is prescribed to treat a bacterial infection, patients should be told that although it is common to feel better early in the course of therapy, the medication should be taken exactly as directed. Skipping doses or not completing the full course of therapy may (1) decrease the effectiveness of the immediate treatment and (2) increase the likelihood that bacteria will develop resistance and will not be treatable by vancomycin hydrochloride for injection, USP or other antibacterial drugs in the future.

Diarrhea is a common problem caused by antibiotics which usually ends when the antibiotic is discontinued. Sometimes after starting treatment with antibiotics, patients can develop watery and bloody stools (with or without stomach cramps and fever) even as late as two or more months after having taken the last dose of the antibiotic. If this occurs, patients should contact their physician as soon as possible.

ADVERSE REACTIONS

Infusion-Related Events

During or soon after rapid infusion of vancomycin hydrochloride for injection, patients may develop anaphylactoid reactions, including hypotension (see ANIMAL PHARMACOLOGY), wheezing, dyspnea, urticaria, or pruritus. Rapid infusion may also cause flushing of the upper body ("red neck") or pain and muscle spasm of the chest and back. These reactions usually resolve within 20 minutes but may persist for several hours. Such events are infrequent if vancomycin hydrochloride for injection is given by a slow infusion over 60 minutes. In studies of normal volunteers, infusion-related events did not occur when vancomycin hydrochloride for injection was administered at a rate of 10 mg/min or less.

Nephrotoxicity

Renal failure, principally manifested by increased serum creatinine or BUN concentrations, especially in patients administered large doses of vancomycin, has been reported rarely. Cases of interstitial nephritis have also been reported rarely. Most of these have occurred in patients who were given aminoglycosides concomitantly or who had preexisting kidney dysfunction. When vancomycin was discontinued, azotemia resolved in most patients.

Gastrointestinal

Onset of pseudomembranous colitis symptoms may occur during or after antibiotic treatment (see WARNINGS).

Ototoxicity

A few dozen cases of hearing loss associated with vancomycin hydrochloride have been reported. Most of these patients had kidney dysfunction or a preexisting hearing loss, or were receiving concomitant treatment with an ototoxic drug. Vertigo, dizziness, and tinnitus have been reported rarely.

Hematopoietic

Reversible neutropenia, usually starting 1 week or more after onset of therapy with vancomycin or after a total dosage of more than 25 g, has been reported for several dozen patients.

Neutropenia appears to be promptly reversible when vancomycin is discontinued. Thrombocytopenia has rarely been reported. Although a causal relationship has not been established, reversible agranulocytosis (granulocytes <500/mm^3) has been reported rarely.

Phlebitis

Inflammation at the injection site has been reported.

Miscellaneous

Infrequently, patients have been reported to have had anaphylaxis, drug fever, nausea, chills, eosinophilia, rashes including exfoliative dermatitis, linear IgA bullous dermatosis, Stevens-Johnson syndrome, toxic epidermal necrolysis, and vasculitis in association with the administration of vancomycin.

Chemical peritonitis has been reported following intraperitoneal administration (see PRECAUTIONS)

Post Marketing Reports

The following adverse reactions have been identified during post-approval use of vancomycin. Because these reactions are reported voluntarily from a population of uncertain size, it is not possible to reliably estimate their frequency or establish a causal relationship to drug exposure.

Skin and Subcutaneous Tissue Disorders

Drug Rash with Eosinophilia and Systemic Symptoms (DRESS)

To report SUSPECTED ADVERSE EVENTS, contact FDA at 1-800-FDA-1088 or www.fda.gov.

OVERDOSAGE

Supportive care is advised, with maintenance of glomerular filtration. Vancomycin is poorly removed by dialysis. Hemofiltration and hemoperfusion with polysulfone resin have been reported to result in increased vancomycin clearance.

The median lethal intravenous dose is 319 mg/kg in rats and 400 mg/kg in mice.

To obtain up-to-date information about the treatment of overdose, a good resource is your certified Regional Poison Control Center. Telephone numbers of certified poison control centers are listed in the Physicians' Desk Reference (PDR).In managing overdosage, consider the possibility of multiple drug overdoses, interaction among drugs, and unusual drug kinetics in your patient.

DOSAGE AND ADMINISTRATION

Infusion-related events are related to both the concentration and the rate of administration of vancomycin. Concentrations of no more than 5 mg/mL and rates of no more than 10 mg/min are recommended in adults (see also age-specific recommendations).

In selected patients in need of fluid restriction, a concentration up to 10 mg/mL may be used; use of such higher concentrations may increase the risk of infusion-related events. An infusion rate of 10 mg/min or less is associated with fewer infusion-related events (see ADVERSE REACTIONS). Infusion-related events may occur, however, at any rate or concentration.

Adults

The usual daily intravenous dose is 2 g divided either as 500 mg every 6 hours or 1 g every 12 hours. Each dose should be administered at no more than 10 mg/min, or over a period of at least 60 minutes, whichever is longer. Other patient factors, such as age or obesity, may call for modification of the usual intravenous daily dose.

Pediatric Patients

The usual intravenous dosage of vancomycin is 10 mg/kg per dose given every 6 hours. Each dose should be administered over a period of at least 60 minutes. Close monitoring of serum concentrations of vancomycin may be warranted in these patients.

Neonates

In pediatric patients up to the age of 1 month, the total daily intravenous dosage may be lower. In neonates, an initial dose of 15 mg/kg is suggested, followed by 10 mg/kg every 12 hours for neonates in the 1st week of life and every 8 hours thereafter up to the age of 1 month. Each dose should be administered over 60 minutes. In premature infants, vancomycin clearance decreases as postconceptional age decreases. Therefore, longer dosing intervals may be necessary in premature infants. Close monitoring of serum concentrations of vancomycin is recommended in these patients.

Patients With Impaired Renal Function and Elderly Patients

Dosage adjustment must be made in patients with impaired renal function. In premature infants and the elderly, greater dosage reductions than expected may be necessary because of decreased renal function. Measurement of vancomycin serum concentrations can be helpful in optimizing therapy, especially in seriously ill patients with changing renal function. Vancomycin serum concentrations can be determined by use of microbiologic assay, radioimmunoassay, fluorescence polarization immunoassay, fluorescence immunoassay, or high-pressure liquid chromatography. If creatinine clearance can be measured or estimated accurately, the dosage for most patients with renal impairment can be calculated using the following table. The dosage of vancomycin hydrochloride for injection per day in mg is about 15 times the glomerular filtration rate in mL/min (see following table):

DOSAGE TABLE FOR VANCOMYCIN IN PATIENTS WITH IMPAIRED RENAL FUNCTION
(Adapted from Moellering et al)^4
Creatinine Clearance; mL/min | Vancomycin Dose; mg/24 h
100 | 1,545
90 | 1,390
80 | 1,235
70 | 1,080
60 | 925
50 | 770
40 | 620
30 | 465
20 | 310
10 | 155

The initial dose should be no less than 15 mg/kg, even in patients with mild to moderate renal insufficiency.

The table is not valid for functionally anephric patients. For such patients, an initial dose of 15 mg/kg of body weight should be given to achieve prompt therapeutic serum concentrations. The dose required to maintain stable concentrations is 1.9 mg/kg/24 hr. In patients with marked renal impairment, it may be more convenient to give maintenance doses of 250 to 1,000 mg once every several days rather than administering the drug on a daily basis. In anuria, a dose of 1,000 mg every 7 to 10 days has been recommended.

When only serum creatinine is known, the following formula (based on sex, weight, and age of the patient) may be used to calculate creatinine clearance. Calculated creatinine clearances (mL/min) are only estimates. The creatinine clearance should be measured promptly.

Men: | Weight (kg) x (140- age in years); 72 x serum creatinine concentration (mg/dL)
Women: | 0.85 x above value

The serum creatinine must represent a steady state of renal function. Otherwise, the estimated value for creatinine clearance is not valid. Such a calculated clearance is an overestimate of actual clearance in patients with conditions: (1) characterized by decreasing renal function, such as shock, severe heart failure, or oliguria; (2) in which a normal relationship between muscle mass and total body weight is not present, such as obese patients or those with liver disease, edema, or ascites; and (3) accompanied by debilitation, malnutrition, or inactivity.

The safety and efficacy of vancomycin administration by the intrathecal (intralumbar or intraventricular) routes have not been established.

Intermittent infusion is the recommended method of administration.

Compatibility with Other Drugs and IV Fluids

The following diluents are physically and chemically compatible (with 4 g/L vancomycin hydrochloride):

5% Dextrose Injection, USP

5% Dextrose Injection and 0.9% Sodium Chloride Injection, USP

Lactated Ringer’s Injection, USP

5% Dextrose and Lactated Ringer’s Injection

0.9% Sodium Chloride Injection, USP

Good professional practice suggests that compounded admixtures should be administered as soon after preparation as is feasible.

Vancomycin solution has a low pH and may cause physical instability of other compounds.

Preparation and Stability

At the time of use, reconstitute the vials of Vancomycin Hydrochloride for Injection, USP with Sterile Water for Injection to a concentration of 50 mg of vancomycin/mL (see following table for volume of diluent).

Concentration/Vial | Volume of Diluent
500 mg | 10 mL
1 g | 20 mL

After reconstitution, the vials may be stored in a refrigerator for 96 hours without significant loss of potency.

Reconstituted solutions of vancomycin (500 mg/10 mL) must be further diluted in at least 100 mL of a suitable infusion solution. For doses of 1 gram (20 mL), at least 200 mL of solution must be used. The desired dose diluted in this manner should be administered by intermittent IV infusion over a period of at least 60 minutes.

Parenteral drug products should be visually inspected for particulate matter and discoloration prior to administration, whenever solution and container permit.

Compatibility with Intravenous Fluids

Solutions that are diluted with 5% Dextrose Injection or 0.9% Sodium Chloride Injection may be stored in a refrigerator for 14 days without significant loss of potency. Solutions that are diluted with the following infusion fluids may be stored in a refrigerator for 96 hours:

5% Dextrose Injection and 0.9% Sodium Chloride Injection USP

Lactated Ringer’s Injection USP

Lactated Ringer’s and 5% Dextrose Injection USP

Vancomycin solution has a low pH and may cause chemical or physical instability when it is mixed with other compounds.

Mixtures of solutions of vancomycin and beta-lactam antibiotics have been shown to be physically incompatible. The likelihood of precipitation increases with higher concentrations of vancomycin. It is recommended to adequately flush the intravenous lines between the administration of these antibiotics. It is also recommended to dilute solutions of vancomycin to 5 mg/mL or less.

Although intravitreal injection is not an approved route of administration for vancomycin, precipitation has been reported after intravitreal injection of vancomycin and ceftazidime for endophthalmitis using different syringes and needles. The precipitates dissolved gradually, with complete clearing of the vitreous cavity over two months and with improvement of visual acuity.

Parenteral drug products should be visually inspected for particulate matter and discoloration prior to administration, whenever solution and container permit.

For Oral Administration

Oral vancomycin is used in treating antibiotic-associated pseudomembranous colitis caused by C. difficileand for staphylococcal enterocolitis. Vancomycin is not effective by the oral route for other types of infections. The usual adult total daily dosage is 500 mg to 2 g given in 3 or 4 divided doses for 7 to 10 days. The total daily dose in children is 40 mg/kg of body weight in 3 or 4 divided doses for 7 to 10 days. The total daily dosage should not exceed 2g. The appropriate dose may be diluted in 1 oz of water and given to the patients to drink. Common flavoring syrups may be added to the solution to improve the taste for oral administration. The diluted solution may be administered via a nasogastric tube.

HOW SUPPLIED

Vancomycin Hydrochloride for Injection, USP is supplied as a sterile powder in single-dose fliptop vials that contain the vancomycin equivalent to 500 mg, individually packaged in a carton.

500 mg single-vial (NDC 87188-201-01); Package of 10 vials (NDC 87188-201-90)

Vancomycin Hydrochloride for Injection, USP is supplied as a sterile powder in single-dose fliptop vials that contain the vancomycin equivalent to 1 g, individually packaged in a carton.

1 g single-vial (NDC 87188-202-01); Package of 10 vials (87188-202-90)

NDC Number | Fill
87188-201-01 | 500 mg
87188-202-01 | 1 g

Prior to reconstitution, store dry powder at 20° to 25°C (68° to 77°F) [see USP Controlled Room Temperature].

ANIMAL PHARMACOLOGY

In animal studies, hypotension and bradycardia occurred in dogs receiving an intravenous infusion of vancomycin hydrochloride 25 mg/kg, at a concentration of 25 mg/mL and an infusion rate of 13.3 mL/min.

REFERENCES

1.Moellering RC, Krogstad DJ, Greenblatt DJ: Vancomycin therapy in patients with impaired renal function: A nomogram for dosage. Ann Inter Med 1981;94:343.

Revised: Apirl, 2026

Distributed by Plano Pharmaceuticals Inc.

125 S Wilke Rd. suite 353, Arlington Heights, IL 60005

Principal Display Panel

Single-dose Filptop Vial

Sterile Powder

Rx only

NDC 87188-202-01

Vancomycin

Hydrochloride for Injection, USP

For Intravenous Use

Equivalent to 1 g/vial Vancomycin

MUST BE FUTHER DILUTED BEFORE USE. SEE PACKAGE INSERT.

Distributed by Plano Pharmaceuticals Inc.

125 S Wilke Rd. suite 353, Arlington Heights, IL 60005

IMPORTANT: Read insert for precautions and directions before use. May contain HCl and/or NaOH for pH adjustment.

Usual Adult Dosage: 2 g daily. Dilute with 20 mL of Sterile Water for Injection.

AFTER DILUTION-REFRIGERATE

Prior to Reconstitution: Store at 20o to 25oC (68o to 77oF) [See USP Controlled Room Temperature].

Lyophilized

Single-dose Filptop Vials

Sterile Powder

Rx only NDC 87188-202-90

Contains 10 of NDC 87188-202-01

Vancomycin

Hydrochloride for Injection, USP

For Intravenous Use

Equivalent to 1 g/vial Vancomycin

MUST BE FUTHER DILUTED BEFORE USE. SEE PACKAGE INSERT.

Plano

For Intravenous Use

IMPORTANT: Read package insert for precautions and directions before use. May contain hydrochloric acid and/or sodium hydroxide for pH adjustment.

Usual Adult Dosage: 2 g daily.

Dilute with 20 mL of Sterile Water for Injection.

Prior to Reconstitution: Store at 20o to 25oC (68o to 77oF) [See USP Controlled Room Temperature].

After Reconstitution: May be stored in a refrigerator for 14 days without significant loss of potency.

Lyophilized.

Distributed by Plano Pharmaceuticals Inc.

125 S Wilke Rd. suite 353, Arlington Heights, IL 60005

Lot

Exp

SIN

GTIN

Single-dose Filptop Vials

10 Units/NDC 87188-202-90

Sterile Powder

Vancomycin

Hydrochloride for Injection, USP

For Intravenous Use

Equivalent to 1 g/vial Vancomycin

MUST BE FUTHER DILUTED BEFORE USE. SEE PACKAGE INSERT.